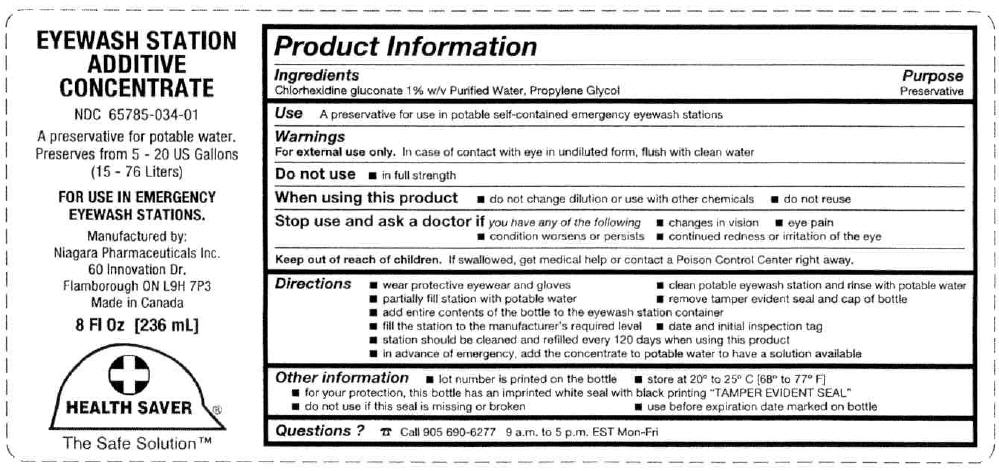 DRUG LABEL: Eyewash Station Additive Concentrate
NDC: 65785-034 | Form: LIQUID
Manufacturer: Niagara Pharmaceuticals Inc.
Category: otc | Type: HUMAN OTC DRUG LABEL
Date: 20251124

ACTIVE INGREDIENTS: CHLORHEXIDINE GLUCONATE 145.6 kg/2800 L; PROPYLENE GLYCOL 280 kg/2800 L
INACTIVE INGREDIENTS: WATER 2374.4 L/2800 L

EYEWASH STATION
ADDITIVE
CONCENTRATE

Product Information

Ingredients

INACTIVE INGREDIENT

Chlorhexidine gluconate 1% w/v Purified Water, Propylene Glycol

Purpose

Preservative

Use

A preservative for use in potable self-contained emergency eyewash stations

Warnings

For external use only.In case of contact with eye in undiluted form, flush with clean water

Do not use

- in full strength

When using this product

- do not change dilution or use with other chemicals
- do not reuse

Stop use and ask a doctor ifyou have any of the following

- changes in vision
- eye pain
- condition worsens or persists
- continued redness or irritation of the eye

Keep out of reach of children.If swallowed, get medical help or contact a Poison Control Center right away.

Directions

- wear protective eyewear and gloves
- clean potable eyewash station and rinse with potable water
- partially fill station with potable water
- remove tamper evident seal and cap of bottle
- add entire contents of the bottle to the eyewash station container
- fill the station to the manufacturer's required level
- date and initial inspection tag
- station should be cleaned and refilled every 120 days when using this product
- in advance of emergency, add the concentrate to potable water to have a solution available

Other information

- lot number is printed on the bottle
- store at 20° to 25° C [68° to 77° F]
- for your protection, this bottle has an imprinted white seal with black printing "TAMPER EVIDENT SEAL"
- do not use if this seal is missing or broken
- use before expiration date marked on bottle

Questions ?

☎ Call 905 690-6277 9 a.m. to 5 p.m. EST Mon-Fri

Manufactured by:
Niagara Pharmaceuticals Inc.
60 Innovation Dr.
Flamborough ON L9H 7P3

PRINCIPAL DISPLAY PANEL - 236 mL Bottle Label

EYEWASH STATION
ADDITIVE
CONCENTRATE

NDC 65785-034-01

A preservative for potable water.
Preserves from 5 - 20 US Gallons
(15 - 76 Liters)

FOR USE IN EMERGENCY
EYEWASH STATIONS.

Manufactured by:
Niagara Pharmaceuticals Inc.
60 Innovation Dr.
Flamborough ON L9H 7P3
Made in Canada

8 Fl Oz [236 mL]

HEALTH SAVER®

The Safe Solution™